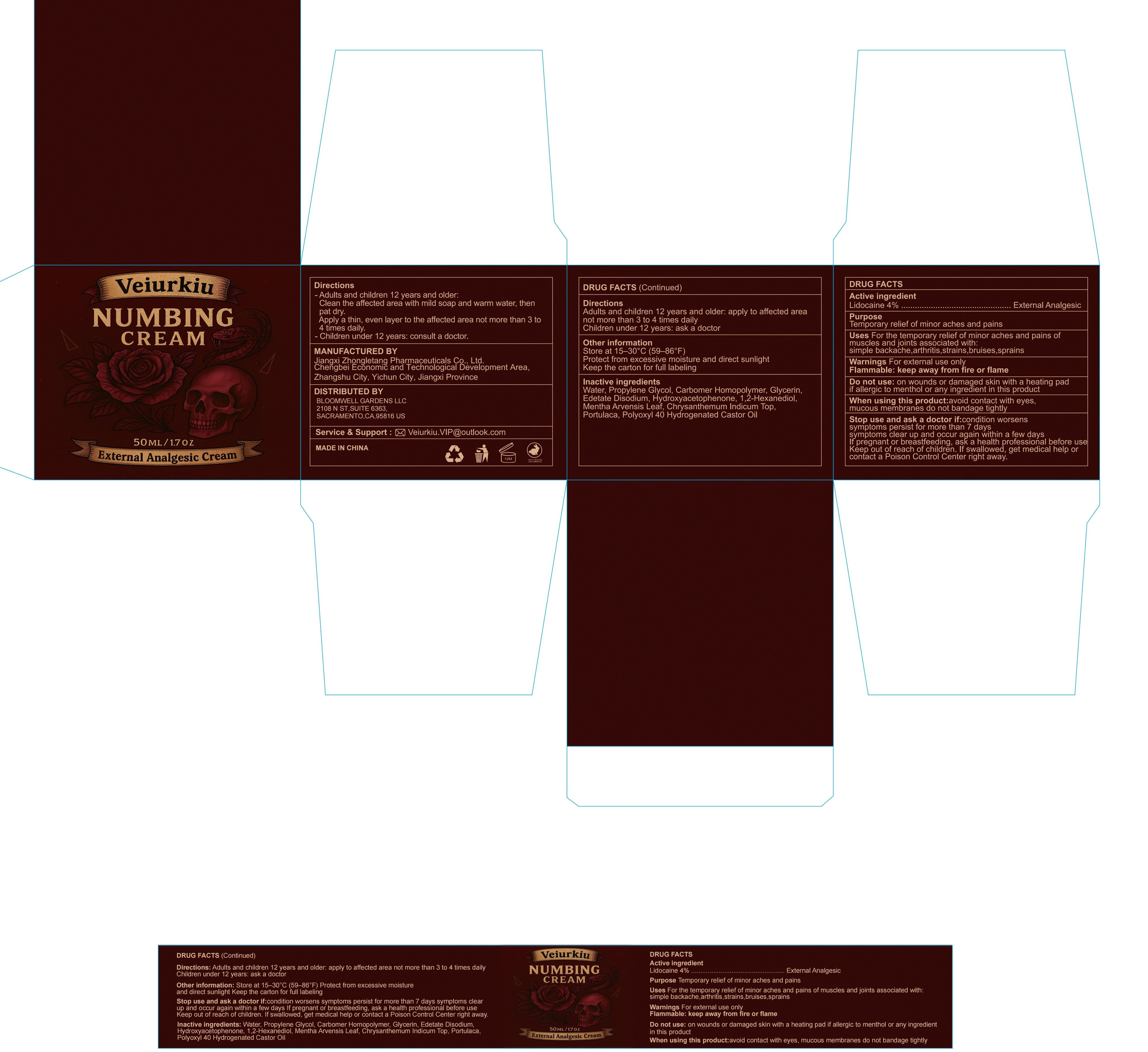 DRUG LABEL: Veiurkiu External Analgesic Cream
NDC: 85284-011 | Form: CREAM
Manufacturer: BLOOMWELL GARDENS LLC
Category: otc | Type: HUMAN OTC DRUG LABEL
Date: 20260218

ACTIVE INGREDIENTS: LIDOCAINE 4 g/100 g
INACTIVE INGREDIENTS: WATER; GLYCERIN; HYDROXYACETOPHENONE; PORTULACA GRANDIFLORA WHOLE; MENTHA ARVENSIS LEAF; EDETATE DISODIUM; 1,2-HEXANEDIOL; CHRYSANTHEMUM INDICUM TOP; PROPYLENE GLYCOL; CARBOMER HOMOPOLYMER, UNSPECIFIED TYPE; POLYOXYL 40 HYDROGENATED CASTOR OIL

Active ingredient

Lidocaine 4%

INACTIVE INGREDIENT

Water, Propylene Glycol, Carbomer Homopolymer, Glycerin,

Edetate Disodium, Hydroxyacetophenone, 1,2-Hexanediol,

Mentha Arvensis Leaf, Chrysanthemum Indicum Top,

Portulaca, Polyoxyl 40 Hydrogenated Castor Oil

PURPOSE

Temporary relief of minor aches and pains

INDICATIONS AND USAGE

For the temporary relief of minor aches and pains of muscles and joints associated with: simple backache, arthritis, strains, bruises, sprains

WARNINGS

For external use only

Flammable: keep away from fire or flame

Stop use and ask a doctor if: condition worsens

symptoms persist for more than 7 days

symptoms clear up and occur again within a few days

Keep out of reach of children. If swallowed, get medical help or

contact a Poison Control Center right away.

PREGNANCY OR BREAST FEEDING

If pregnant or breastfeeding, ask a health professional before use

Do not use: on wounds or damaged skin with a heating pad

if allergic to menthol or any ingredient in this product

When using this product: avoid contact with eyes,

mucous membranes do not bandage tightly

Directions

Adults and children 12 years and older: apply to affected area

not more than 3 to 4 times daily

Children under 12 years: ask a doctor

OTHER SAFETY INFORMATION

Store at 15–30°C (59–86°F)

Protect from excessive moisture and direct sunlight

Keep the carton for full labeling

PACKAGE LABEL

Cream Lidocaine -011